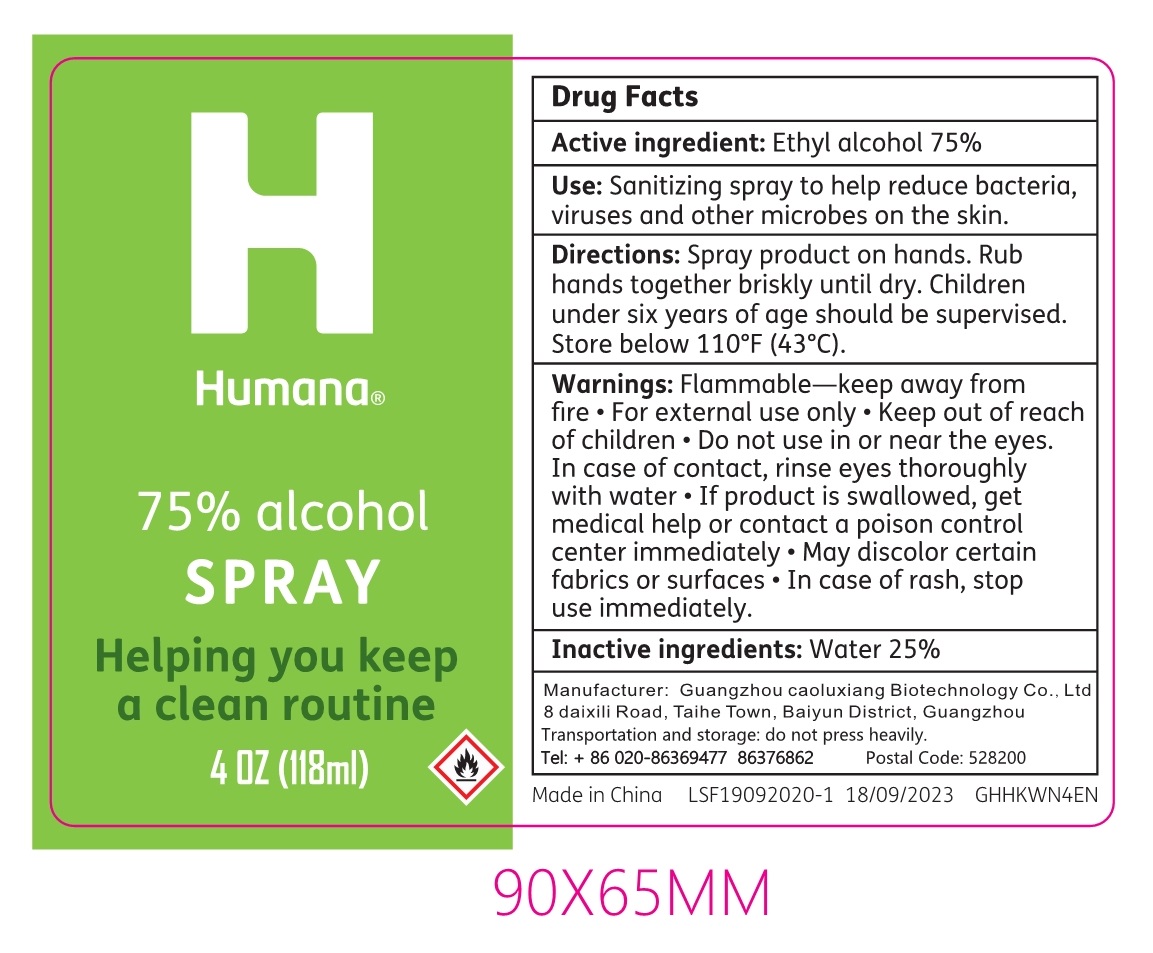 DRUG LABEL: 75% alcohol
NDC: 78414-005 | Form: SPRAY
Manufacturer: Guangzhou caolvxiang Biotechnology Co.,Ltd
Category: otc | Type: HUMAN OTC DRUG LABEL
Date: 20200918

ACTIVE INGREDIENTS: ALCOHOL 75 mL/100 mL
INACTIVE INGREDIENTS: WATER

78414-005
75% alcohol SPRAY

Active Ingredient(s)

Ethyl Alcohol75%

Purpose

Antiseptic

Use

Sanitizing spray to help reduce bacteria, viruses and other microbes on the skin.

Warnings

Flammable—keep away from fire
For external use only

Keep out of reach of children

Do not use in or near the eyes.
In case of contact, rinse eyes thoroughly with water
If product is swallowed, get medical help or contact a poison control center immediately

May discolor certain fabrics or surfaces
In case of rash, stop use immediately.

Do not use in or near the eyes.
In case of contact, rinse eyes thoroughly with water
If product is swallowed, get medical help or contact a poison control center immediately

WHEN USING SECTION

Keep out of reach of children

Do not use in or near the eyes.
In case of contact, rinse eyes thoroughly with water
If product is swallowed, get medical help or contact a poison control center immediately

May discolor certain fabrics or surfaces
In case of rash, stop use immediately.

STOP USE

May discolor certain fabrics or surfaces
In case of rash, stop use immediately.

Keep out of reach of children

Directions

Spray product on hands. Rub hands together briskly until dry. Children under six years of age should be supervised. Store below 110°F (43°C).

Other information

/

Inactive ingredients

Water